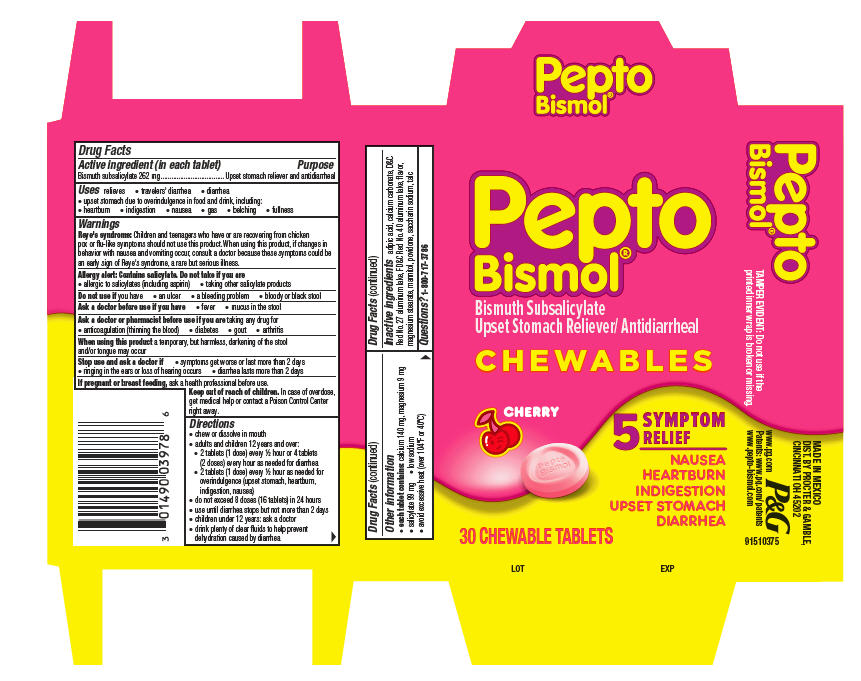 DRUG LABEL: Pepto Bismol
NDC: 58933-013 | Form: TABLET, CHEWABLE
Manufacturer: Procter & Gamble Manufactura S de RL de CV
Category: otc | Type: HUMAN OTC DRUG LABEL
Date: 20251001

ACTIVE INGREDIENTS: BISMUTH SUBSALICYLATE 525 mg/2 1
INACTIVE INGREDIENTS: D&C RED NO. 27 ALUMINUM LAKE; SACCHARIN SODIUM; TALC; CALCIUM CARBONATE; MAGNESIUM STEARATE; MANNITOL; POVIDONE; ALUMINUM OXIDE; ADIPIC ACID; FD&C RED NO. 40 ALUMINUM LAKE

Pepto Bismol®
CHEWABLES

Drug Facts

Active ingredient (in each tablet)

Bismuth subsalicylate 262 mg

Active ingredient (in each tablet) Purpose

Upset stomach reliever and antidiarrheal

Uses

relieves

- travelers' diarrhea
- diarrhea
- upset stomach due to overindulgence in food and drink, including:
  - heartburn
  - indigestion
  - nausea
  - gas
  - belching
  - fullness

Warnings

Reye's syndrome:Children and teenagers who have or are recovering from chicken pox or flu-like symptoms should not use this product.When using this product, if changes in behavior with nausea and vomiting occur, consult a doctor because these symptoms could be an early sign of Reye's syndrome, a rare but serious illness.

Allergy alert: Contains salicylate. Do not take if you are
• allergic to salicylates (including aspirin) • taking other salicylate products

Do not use if

you have

- an ulcer
- a bleeding problem
- bloody or black stool

Ask a doctor before use if you have

- fever
- mucus in the stool

Ask a doctor or pharmacist before use if you are

taking any drug for

- anticoagulation (thinning the blood)
- diabetes
- gout
- arthritis

When using this product

a temporary, but harmless, darkening of the stool and/or tongue may occur

Stop use and ask a doctor if

- symptoms get worse or last more than 2 days
- ringing in the ears or loss of hearing occurs
- diarrhea lasts more than 2 days

PREGNANCY OR BREAST FEEDING

If pregnant or breast feeding,ask a health professional before use.

Keep out of reach of children.

OVERDOSAGE

In case of overdose, get medical help or contact a Poison Control Center right away.

Directions

- chew or dissolve in mouth
- adults and children 12 years and over: 2 tablets (1 dose) every 1/2 hour or 4 tablets (2 doses) every hour as needed for diarrhea
- 2 tablets (1 dose) every ½ hour as needed for overindulgence (upset stomach, heartburn, indigestion, nausea)
- do not exceed 8 doses (16 tablets) in 24 hours
- use until diarrhea stops but not more than 2 days
- children under 12 years: ask a doctor
- drink plenty of clear fluids to help prevent dehydration caused by diarrhea

Other information

- each tablet contains:calcium 140 mg, magnesium 9 mg
- salicylate 99 mg
- low sodium
- avoid excessive heat (over 104°F or 40°C)

Inactive ingredients

adipic acid, calcium carbonate, D&C Red No. 27 aluminum lake, FD&C Red No. 40 aluminum lake, flavor, magnesium stearate, mannitol, povidone, saccharin sodium, talc

Questions?

1-800-717-3786

TAMPER EVIDENT: Do not use if the printed inner wrap is broken or missing.

MADE IN MEXICO

DIST. BY PROCTER & GAMBLE

CINCINNATI, OH 45202

PRINCIPAL DISPLAY PANEL - 30 Tablet Carton

Pepto
Bismol ®

Bismuth Subsalicylate
Upset Stomach Reliever/ Antidiarrheal

CHEWABLES

CHERRY

5 SYMPTOM

RELIEF

NAUSEA
HEARTBURN
INDIGESTION
UPSET STOMACH
DIARRHEA

30 CHEWABLE TABLETS